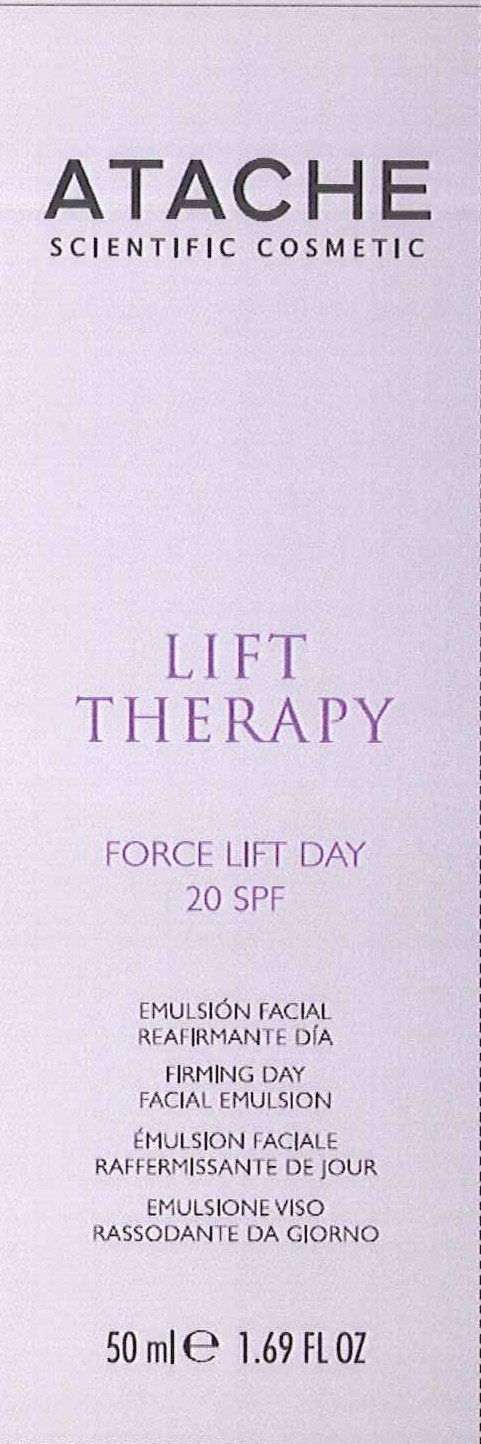 DRUG LABEL: LIFT THERAPY FORCE LIFT DAY 20 SPF
NDC: 75870-001 | Form: CREAM
Manufacturer: LABORATORIOS DE COSMETICA SCIENTIFICA ATACHE SA
Category: otc | Type: HUMAN OTC DRUG LABEL
Date: 20110616

ACTIVE INGREDIENTS: OCTOCRYLENE 5 mL/50 mL; OCTINOXATE 3.75 mL/50 mL; AVOBENZONE 1.75 mL/50 mL
INACTIVE INGREDIENTS: WATER; GLYCERIN; TRIBEHENIN PEG-20 ESTERS; ALUMINUM STARCH OCTENYLSUCCINATE; MEDIUM-CHAIN TRIGLYCERIDES; CETYL ALCOHOL; ALKYL (C12-15) BENZOATE; CYCLOMETHICONE 5; ALCOHOL; ALPHA-TOCOPHEROL; XANTHAN GUM; POLYSORBATE 80; CARBOMER COPOLYMER TYPE A; LECITHIN, SOYBEAN; SOY ISOFLAVONES; ACMELLA OLERACEA FLOWER; PHENOXYETHANOL; BENZOIC ACID; SODIUM HYDROXIDE; DEHYDROACETIC ACID; ETHYLHEXYLGLYCERIN; POLYAMINOPROPYL BIGUANIDE

LIFT THERAPY FORCE LIFT DAY 20 SPF

PACKAGE LABEL

LIFT THERAPY
FORCE LIFT DAY
20 SPF
FIRMING DAY
FACIAL EMULSION
50 ml 1.69 FL OZ

DESCRIPTION

Gives skin a visibly lifted look and provides advanced UVA/UVB sun protection to help prevent premature skin aging. The silky textured moisturizer combines Glatuline In-Tense and Soy Isoflavones to help visibly firm and tone skin.

INSTRUCTIONS FOR USE

Directions: Apply each morning to the face before cleansing and toning with the ATACHE products most suited to your skin. Gently massage with upward strokes until fully absorbed.

WARNINGS

Warning: For external use only. Keep out of reach of children. Avoid direct contact with eyes. Discontinue use if signs of irrigation appear.

ACTIVE INGREDIENTS:
OCTOCRYLENE 10% - sunscreen
ETHYLHEXYL METHOXYCINNAMATE 7,5% - sunscreen
AVOBENZONE 3.5% - sunscreen

INACTIVE INGREDIENT

OTHER INGREDIENTS: AQUA, GLYCERIN, TRIBEHENIN PEG-20 ESTERS, ALUMINUM STARCH OCTENYLSUCCINATE, CAPRYLIC/CAPTICTRIGLYCERIDE, CETYL ALCOHOL C12-15 ALKYL BENZOATE, CYCLOPENTASILOXANE, ALCOHOLTOCOPHERYL ACETATE XANTHAN GUM, POLYSORBATE 80, ACRYLATES/C10-30 ALKYL ACRYLATE CROSSPOLYMER, LECITHIN, PARFUM, SOY ISOFLAVONES, SPILANTHES ACMELLA FLOWER EXTRACT, PHENOXYETHANOL, BENZOIC ACID, DISODIUM EDTA, SODIUM HYDROXIDE, DEHYDROACETIC ACID, ETHYLHEXYLGLYCERIN, POLAMINOPROPYL BIGUANIDE.